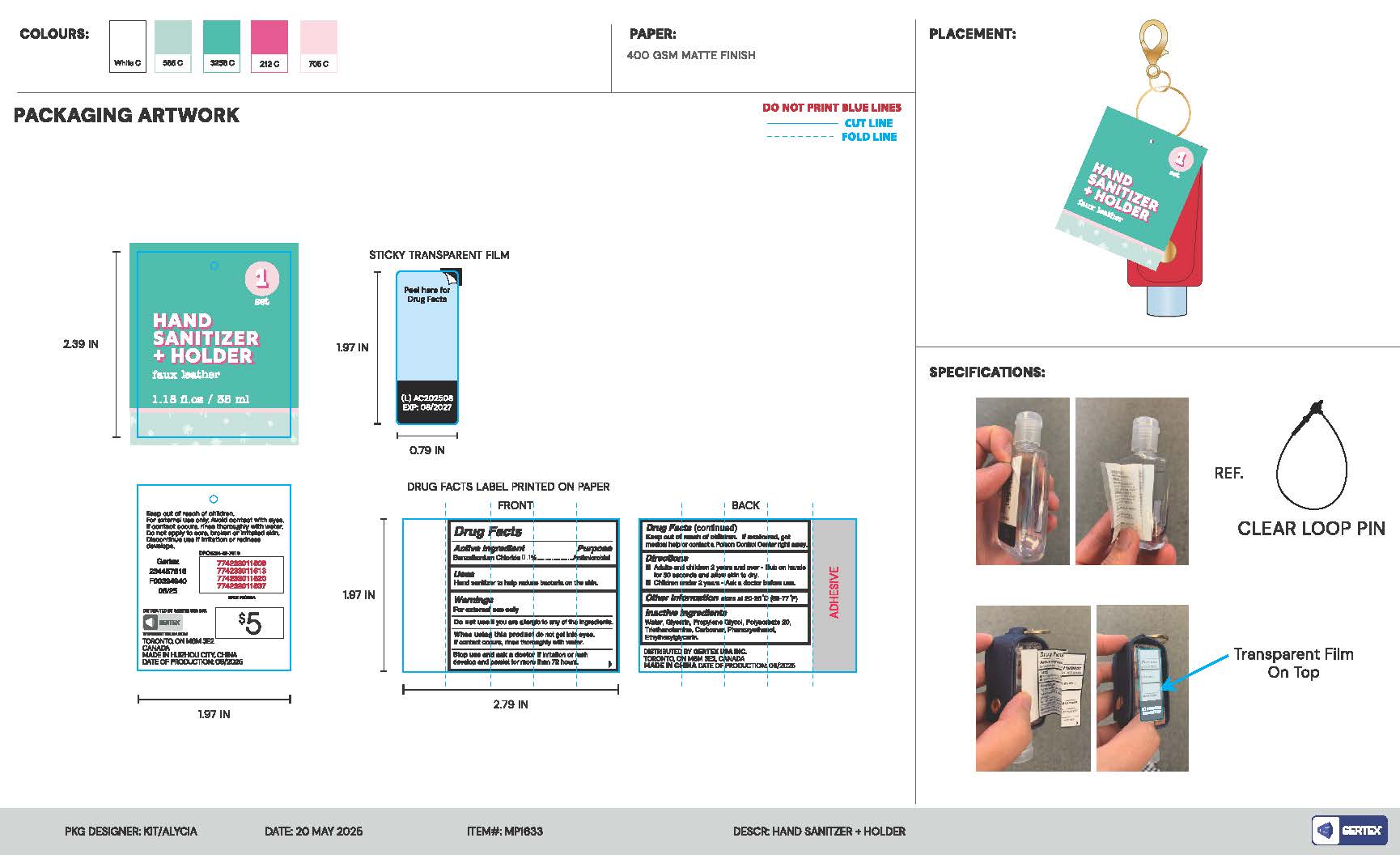 DRUG LABEL: Hand Sanitizer plus Holder
NDC: 87129-100 | Form: LIQUID
Manufacturer: Aocai Biotechnology Huizhou Co Ltd
Category: otc | Type: HUMAN OTC DRUG LABEL
Date: 20250925

ACTIVE INGREDIENTS: BENZALKONIUM CHLORIDE 0.1 g/1 mL
INACTIVE INGREDIENTS: WATER; GLYCERIN; PROPYLENE GLYCOL; POLYSORBATE 20; TRIETHANOLAMINE; CARBOMER; PHENOXYETHANOL; ETHYLHEXYLGLYCERIN

Hand Sanitizer plus Holder

Active Ingredient

Benzalkonium Chloride 0.1%

Purpose

Antimicrobial

Uses

Hand sanitizer to help reduce bacteria on the skin.

Warnings

For External use only.

Do not use

if you are allergic to any of the ingredients.

When using this product

do not get into eyes. If contact occurs, rinse thoroughly with water.

Stop use and ask a doctor.

If irritation or rash occurs develop and persist for more than 72 hours.

Keep out of reach of children.

If swallowed, get medical help or contact a Poison Control Center right away.

Directions

-Adults and children 2 years and over.

-Rub on hands for 30 seconds and allow skin to dry.

-Children under 2 years.

-Ask a doctor before use.

Other Information

Store at 20-25C (68-77F)

Inactive Ingredients

Water, Glycerin, Propylene Glycol, Polysorbate 20, Triethanolamine, Carbomer, Phenoxyethanol, Ethylhexylglycerin.